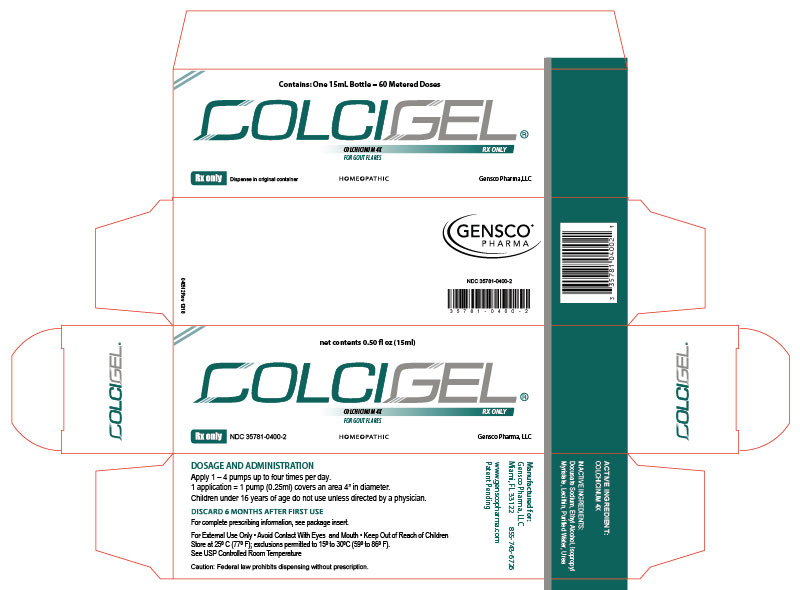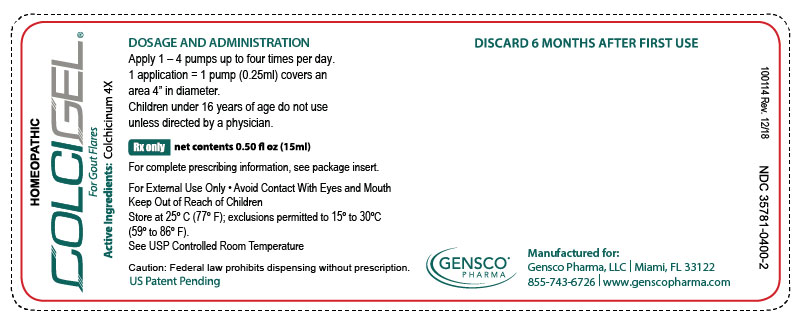 DRUG LABEL: COLCIGEL
NDC: 35781-0400 | Form: GEL
Manufacturer: Gensco Laboratories, LLC
Category: homeopathic | Type: HUMAN PRESCRIPTION DRUG LABEL
Date: 20221004

ACTIVE INGREDIENTS: COLCHICINE 4 [hp_X]/15 mL
INACTIVE INGREDIENTS: ALCOHOL; WATER; ISOPROPYL MYRISTATE; LECITHIN, SOYBEAN; UREA; DOCUSATE SODIUM

HIGHLIGHTS OF PRESCRIBING INFORMATION

COLCIGEL
These highlights do not include all the information needed to use colchicine safely and effectively. See full prescribing information for ColciGel®.
Initial U.S. Approval

1 INDICATIONS AND USAGE

ColciGel® (colchicinum 4X) transdermal gel is an alkaloid indicated for:

Treatment and Prophylaxis of Gout Flares in adults.(1.1)
ColciGel® (colchicinum 4X) is not an analgesic medication and should not be used to treat pain from other causes.

3 DOSAGE FORMS AND STRENGTHS

ColciGel® is Colchicinum 4X in a transdermal gel base. The gel is viscous and opaque in appearance. ColciGel® is available in 15 mL sealed dispensing containers that produce 0.25 mL of gel per each manual depression of the plunger top (pump).

4 CONTRAINDICATIONS

Traumatized skin, secondary bacterial infection of the area of proposed application and known hypersensitivity to any of the components.

FULL PRESCRIBING INFORMATION

1 INDICATIONS AND USAGE

1.1 Gout Flares

ColciGel® transdermal gel is indicated for prophylaxis and the treatment of acute gout flares.

Treatment of Gout Flares:

ColciGel® gel is indicated for treatment of acute gout flares when used at the first sign of a flare.

Prophylaxis of Gout Flares:

ColciGel® is indicated for prophylaxis of gout flares.

2 DOSAGE AND ADMINISTRATION

Apply 1 – 4 pumps up to four times per day.

1 application = 1 pump (0.25ml) covers an area 4” in diameter.

Children under 16 years of age do not use unless directed by a physician.

DISCARD 6 MONTHS AFTER FIRST USE

3 DOSAGE FORMS AND STRENGTHS

ColciGel® is Colchicinum 4X in a transdermal gel base. The gel is viscous and opaque in appearance. ColciGel® is available in 15 mL sealed dispensing containers that produce 0.25 mL of gel per each manual depression of the plunger top (pump).

4 CONTRAINDICATIONS

Patients with severe renal or severe hepatic impairment should not be given ColciGel® in conjunction with P-gp or strong CYP3A4 inhibitors (this includes all protease inhibitors, except fosamprenavir). In these patients, life-threatening and fatal colchicine toxicity has been reported with ORAL colchicine taken in therapeutic doses.

5 WARNINGS

For External Use Only • Avoid Contact With Eyes and Mouth • Keep Out of Reach of Children Store at 25º C (77º F); exclusions permitted to 15º to 30ºC (59º to 86º F). See USP Controlled Room Temperature

PRECAUTIONS

Use in Pregnancy: No human or animal studies on the effect of ColciGel® (colchicinum 4X) in pregnancy have been conducted.

Nursing Mothers: It is not known whether ColciGel® (colchicinum 4X) is excreted in breast milk.

6 ADVERSE REACTIONS

Prophylaxis and Treatment of Gout Flares: The most commonly reported adverse reaction in clinical trials for the prophylaxis and treatment of gout was mild skin irritation at the site of application.

7 DRUG INTERACTIONS

ColciGel® (Colchicinum 4X) is a substrate of the efflux transporter P-glycoprotein (P-gp). Of the cytochrome P450 enzymes tested, CYP3A4 was mainly involved in the metabolism of colchicinum. If ORAL colchicine is administered with drugs that inhibit P-gp, most of which also inhibit CYP3A4, increased concentrations of colchicinum are likely. Fatal drug interactions have been reported. Topical application of ColciGel® has demonstrated insignificant systemic absorption in animal testing and confirmed in limited human pharmacokinetic evaluations and, therefore, poses a limited risk of clinically significant drug interactions. Physicians should, however, ensure that patients are suitable candidates for treatment with ColciGel® and remain alert for signs and symptoms of toxicities related to increased colchicinum exposure as a result of a drug interaction. Signs and symptoms of ColciGel® toxicity should be evaluated promptly and, if toxicity is suspected, ColciGel® should be discontinued immediately.

12 CLINICAL PHARMACOLOGY

The mechanism by which colchicinum exerts its beneficial effect in patients has not been fully elucidated; however, evidence suggests that colchicinum may interfere with the intracellular assembly of the inflammasome complex present in neutrophils and monocytes that mediates activation of interleukin-1alpha. Additionally, colchicine disrupts cytoskeletal functions through inhibition of alpha-tubulin polymerization into microtubules and consequently prevents the activation, degranulation, and migration of neutrophils thought to mediate some gout symptoms.

13 NONCLINICAL TOXICOLOGY

Carcinogenesis

Carcinogenicity studies of colchicinum have not been conducted. Due to the potential for colchicinum to produce aneuploid cells (cells with an unequal number of chromosomes), there is theoretically an increased risk of malignancy..

Mutagenesis

Colchicine was negative for mutagenicity in the bacterial reverse mutation assay. In a chromosomal aberration assay in cultured human white blood cells, colchicine treatment resulted in the formation of micronuclei. Since published studies demonstrated that colchicine induces aneuploidy from the process of mitotic nondisjunction without structural DNA changes, colchicine is not considered clastogenic, although micronuclei are formed.

Impairment of Fertility

No studies of colchicinum effects on fertility were conducted with ColciGel®. However, published nonclinical studies demonstrated that colchicine-induced disruption of microtubule formation affects meiosis and mitosis. Reproductive studies also reported abnormal sperm morphology and reduced sperm counts in males, and interference with sperm penetration, second meiotic division, and normal cleavage in females when exposed to colchicine. Colchicine administered to pregnant animals resulted in fetal death and teratogenicity. These effects were dose dependent, with the timing of exposure critical for the effects on embryofetal development. The nonclinical doses evaluated were generally higher than an equivalent human ORAL therapeutic dose, but safety margins for reproductive and developmental toxicity could not be determined. Case reports and epidemiology studies in human male subjects on colchicine therapy indicated that infertility from colchicine is rare. A case report indicated that azoospermia was reversed when therapy was stopped. Case reports and epidemiology studies in female subjects on colchicine therapy have not established a clear relationship between colchicinum use and female infertility. The use of colchicinum needs to be weighed against the potential risks.

14 HOW SUPPLIED/STORAGE AND HANDLING

14.1 How Supplied

ColciGel® is Colchicinum 4X in a transdermal gel base. The gel is viscous and opaque in appearance. ColciGel® is available in 2x15mL sealed dispensing containers that produce 0.25 mL of gel per each manual depression of the plunger top (pump).
2x15mL (1.01 fl oz) Bottles NDC 35781-0400-4

14.2 Storage

Store at 20° to 25°C (68° to 77°F).
[See USP Controlled Room Temperature]

DISPENSE IN ORIGINAL CONTAINER.

US Patent Pending

Manufactured for:

Gensco Pharma, LLC

8550 NW 33rd Street, Suite 200.

Miami, FL 33122

(855) 743-6726

www.genscopharma.com